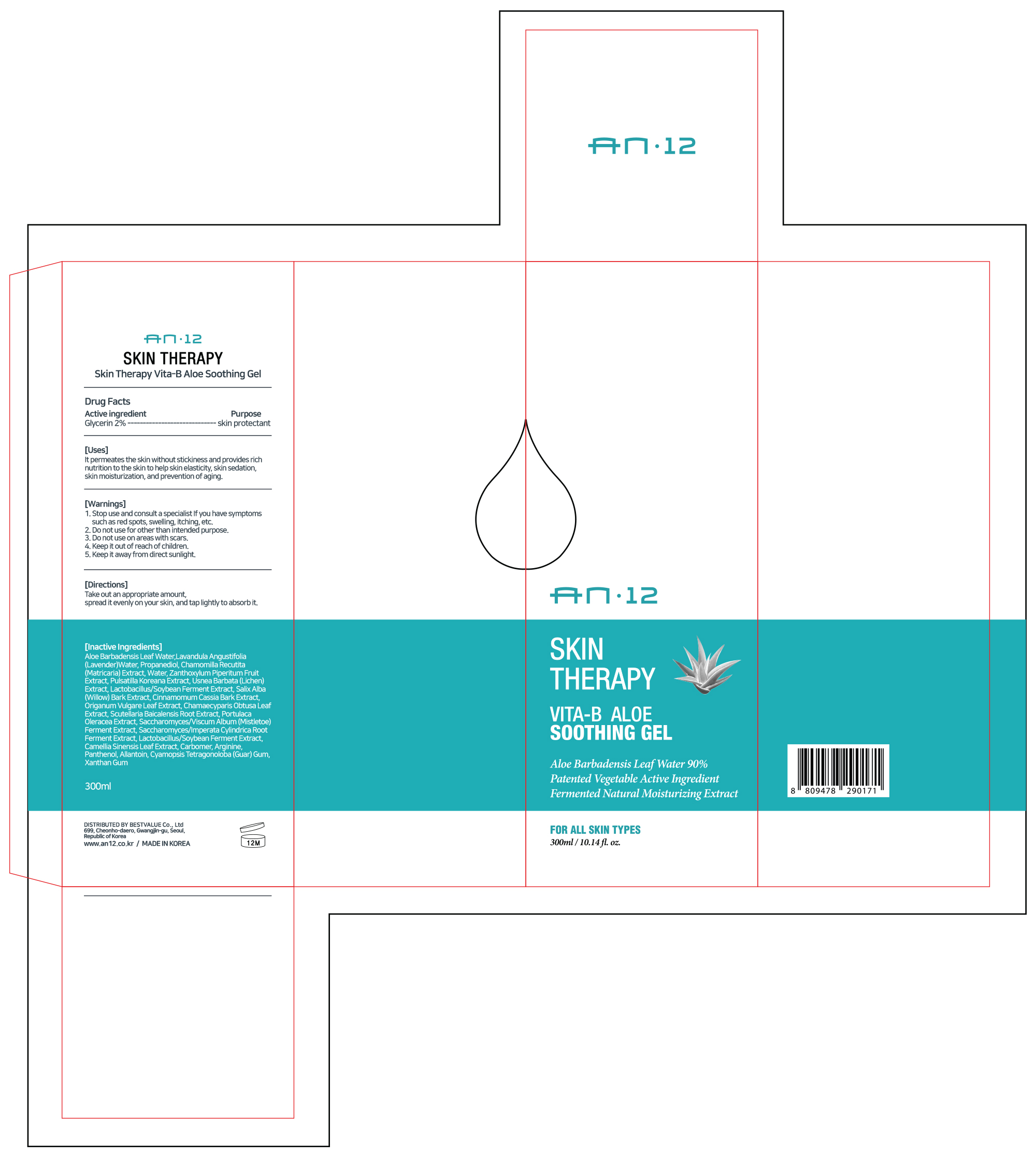 DRUG LABEL: AN12 Skin Therapy Vita-B Aloe Soothing Gel
NDC: 82385-104 | Form: GEL
Manufacturer: BESTVALUE Co., Ltd
Category: otc | Type: HUMAN OTC DRUG LABEL
Date: 20250131

ACTIVE INGREDIENTS: GLYCERIN 2 g/100 mL
INACTIVE INGREDIENTS: ALOE VERA LEAF; LAVENDER OIL; SALIX ALBA BARK; OREGANO; CHAMAECYPARIS OBTUSA LEAF; VISCUM ALBUM FRUITING TOP; GREEN TEA LEAF; ARGININE; WATER; PROPANEDIOL; MATRICARIA CHAMOMILLA WHOLE; SOYBEAN; LACTOBACILLUS ACIDOPHILUS; PULSATILLA KOREANA ROOT; USNEA BARBATA; ZANTHOXYLUM PIPERITUM FRUIT PULP; SCUTELLARIA BAICALENSIS ROOT; GUAR GUM; IMPERATA CYLINDRICA ROOT; CARBOMER HOMOPOLYMER, UNSPECIFIED TYPE; ALLANTOIN; XANTHAN GUM; PANTHENOL

82385-104 AN12 Skin Therapy Vita-B Aloe Soothing Gel

Active Ingredient

Glycerin 2%

Purpose

skin protectant

Uses

It permeates the skin without stickiness and provides rich nutrition to the skin to help skin elasticity, skin sedation, skin moisturization, and prevention of aging.

Warnings

Stop use and consult a specialist If you have symptoms such as red spots, swelling, itching, etc.

Warnings

Do not use for other than intended purpose

Warnings

Do not use on areas with scars.

Warnings

Keep it out of reach of children.

Warnings

Keep it away from direct sunlight.

Directions

Take out an appropriate amount, spread it evenly on your skin, and tap lightly to absorb it.

Inactive Ingredients

Aloe Barbadensis Leaf Water, Lavandula Angustifolia (Lavender) Water, Propanediol,

Chamomilla Recutita (Matricaria) Extract, Water, Zanthoxylum Piperitum Fruit Extract,

Pulsatilla Koreana Extract, Usnea Barbata (Lichen) Extract,

Salix Alba (Willow) Bark Extract, Cinnamomum Cassia Bark Extract, Origanum Vulgare Leaf Extract,

Chamaecyparis Obtusa Leaf Extract, Scutellaria Baicalensis Root Extract,

Portulaca Oleracea Extract, Saccharomyces/Viscum Album (Mistletoe) Ferment Extract

Saccharomyces/Imperata Cylindrica Root Ferment Extract, Camellia Sinensis Leaf Extract, Carbomer, Arginine, Panthenol,

Allantoin, Cyamopsis Tetragonoloba (Guar) Gum, Xanthan Gum